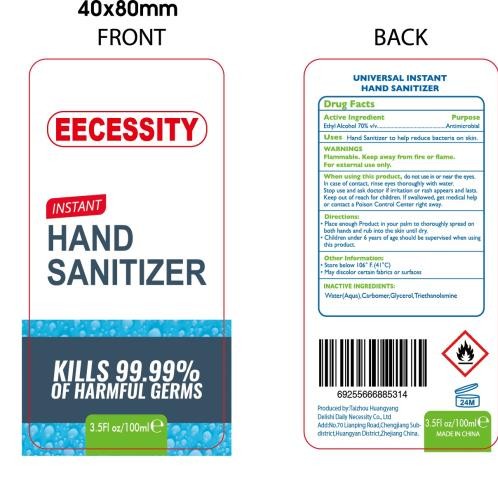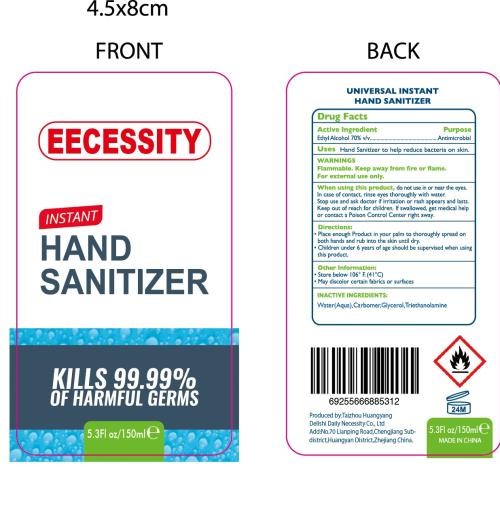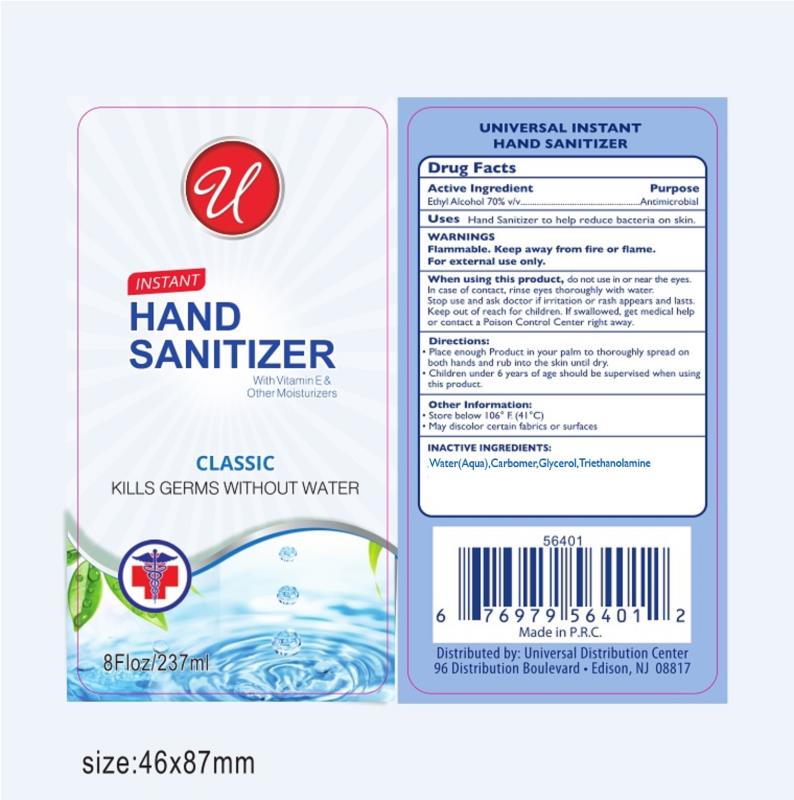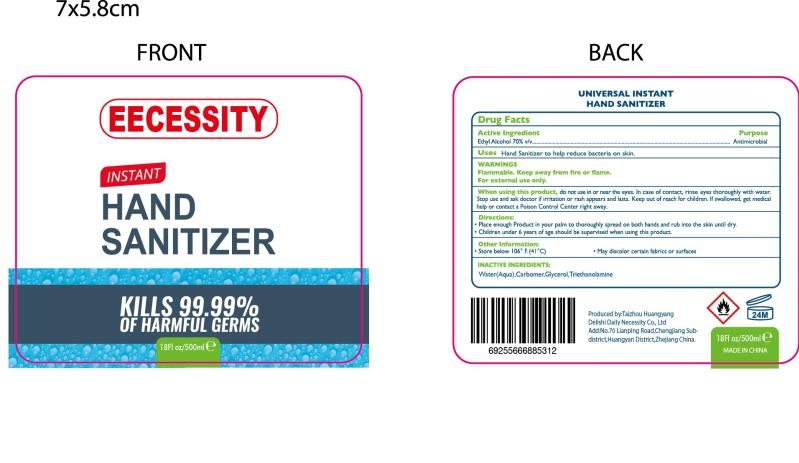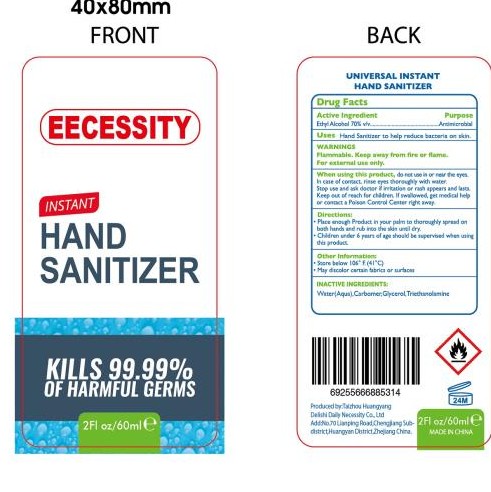 DRUG LABEL: INSTANT HAND SANITIZER
NDC: 76681-005 | Form: GEL
Manufacturer: Taizhou Huangyan Delishi Daily Necessity Co., Ltd.
Category: otc | Type: HUMAN OTC DRUG LABEL
Date: 20200505

ACTIVE INGREDIENTS: ALCOHOL 70 mL/100 mL
INACTIVE INGREDIENTS: GLYCERIN; WATER; CARBOMER HOMOPOLYMER TYPE C (ALLYL PENTAERYTHRITOL CROSSLINKED); TROLAMINE

Active Ingredient(s)

Ethyl Alcohol 70% vlv. Purpose: Antimicrobial

Purpose

Antimicrobial, Hand Sanitizer

Use

Hand Sanitizer to help reduce bacteria on skin

Warnings

Flammable. Keep away from fire or flameFor external use only.

Do not use

/

When using this product keep out of eyes, ears, and mouth. In case of contact with eyes, rinse eyes thoroughly with water.
Stop use and ask a doctor if irritation or rash occurs. These may be signs of a serious condition.
Keep out of reach of children. If swallowed, get medical help or contact a Poison Control Center right away.

STOP USE

/

KEEP OUT OF REACH OF CHILDREN

Children under 6 years of age should be supervised when usingthis product.

Directions

- Directions:Place enough Product in your palm to thoroughly spread on both hands and rub into the skin until dry
  Children under 6 years of age should be supervised when using this product

Other information

- Store below 06F.(4°C)
- May discolor certain fabrics or surfaces

Inactive ingredients

Water(Aqua), Carbomer Glycerol, Triethanolamine